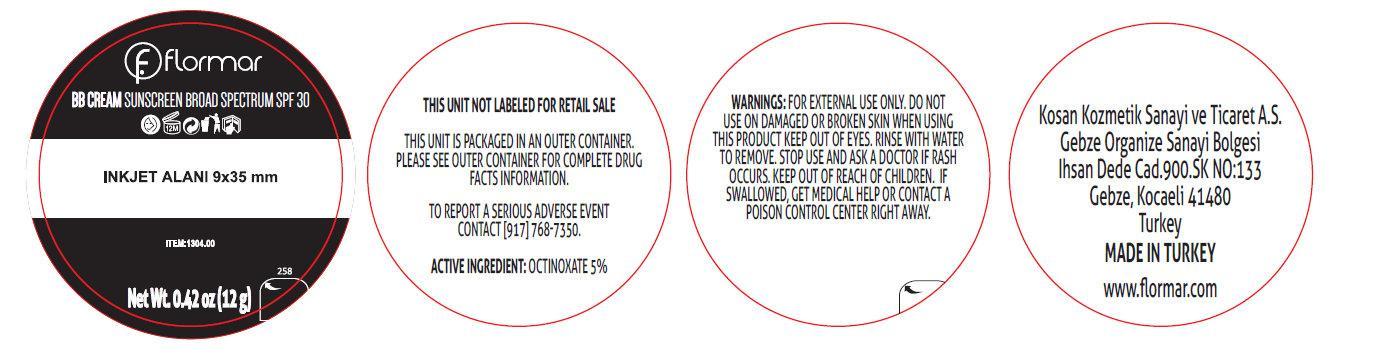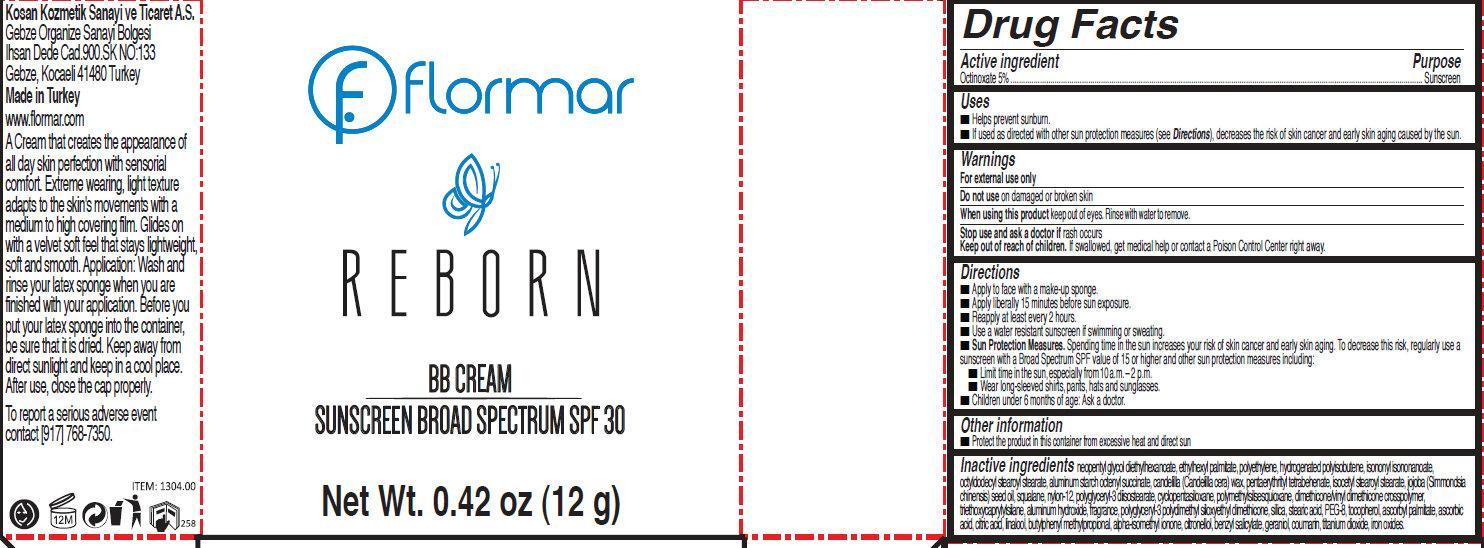 DRUG LABEL: flormar REBORN BB SUNSCREEN BROAD SPECTRUM SPF 30 CP01 Rose
NDC: 61722-160 | Form: CREAM
Manufacturer: Kosan Kozmetik Sanayi ve Ticaret A.S.
Category: otc | Type: HUMAN OTC DRUG LABEL
Date: 20191018

ACTIVE INGREDIENTS: OCTINOXATE 50 mg/1 g
INACTIVE INGREDIENTS: NEOPENTYL GLYCOL DIETHYLHEXANOATE; ETHYLHEXYL PALMITATE; HIGH DENSITY POLYETHYLENE; ISONONYL ISONONANOATE; OCTYLDODECYL STEAROYL STEARATE; ALUMINUM STARCH OCTENYLSUCCINATE; CANDELILLA WAX; PENTAERYTHRITYL TETRABEHENATE; ISOCETYL STEAROYL STEARATE; JOJOBA OIL; SQUALANE; NYLON-12; POLYGLYCERYL-3 DIISOSTEARATE; CYCLOMETHICONE 5; ALUMINUM HYDROXIDE; SILICON DIOXIDE; STEARIC ACID; POLYETHYLENE GLYCOL 400; TOCOPHEROL; ASCORBYL PALMITATE; ASCORBIC ACID; CITRIC ACID MONOHYDRATE; LINALOOL, (+/-)-; BUTYLPHENYL METHYLPROPIONAL; ISOMETHYL-.ALPHA.-IONONE; .BETA.-CITRONELLOL, (R)-; BENZYL SALICYLATE; GERANIOL; COUMARIN; TITANIUM DIOXIDE; FERRIC OXIDE RED

flormar REBORN BB SUNSCREEN BROAD SPECTRUM SPF 30 CP01 Rose

Active ingredient

Octinoxate 5%

Purpose

Sunscreen

Uses

- Helps prevent sunburn.
- If used as directed with other sun protection measures (see Directions), decreases the risk of skin cancer and early skin aging caused by the sun.

Warnings

For external use only

Do not use

on damaged or brokenskin

When using this product

keep out of eyes. Rinse with water to remove.

Stop use and ask a doctor if

rash occurs

Keep out of reach of children.

If swallowed, get medical help or contact a Poison Control Center right away.

Directions

- Apply to face with a make-up sponge.
- Apply liberally 15 minutes before sun exposure.
- Reapply at least every 2 hours.
- Use a water resistant sunscreen if swimming or sweating.
- Sun Protection Measures. Spending time in the sun increases your risk of skin cancer and early skin aging. To decrease this risk, regularly use a sunscreen with a Broad Spectrum SPF value of 15 or higher and other sun protection measures including:
-
  - Limit time in the sun, especially from 10 a.m. – 2 p.m.
  - Wear long-sleeved shirts, pants, hats and sunglasses.
- Children under 6 months of age: Ask a doctor.

Other information

- Protect the product in this container from excessive heat and direct sun

Inactive ingredients

neopentyl glycol diethylhexanoate, ethylhexyl palmitate, polyethylene, hydrogenated polyisobutene, isononyl isononanoate, octyldodecyl stearoyl stearate, aluminum starch octenyl succinate, candelilla (Candelilla cera) wax, pentaerythrityl tetrabehenate, isocetyl stearoyl stearate, jojoba (Simmondsia chinensis) seed oil, squalane, nylon-12, polyglyceryl-3 diisostearate, cyclopentasiloxane, polymethylsilsesquioxane, dimethicone/vinyl dimethicone crosspolymer, triethoxycaprylylsilane, aluminum hydroxide, fragrance, polyglyceryl-3 polydimethyl siloxyethyl dimethicone, silica, stearic acid, PEG-8, tocopherol, ascorbyl palmitate, ascorbic acid, citric acid, linalool, butylphenyl methylpropional, alpha-isomethyl ionone, citronellol, benzyl salicylate, geraniol, coumarin, titanium dioxide, iron oxides

Kosan Kozmetik Sanayi ve Ticaret A.S.

Gebze Organize Sanayi Bolgesi Ihsan Dede Cad.900.SK NO:133 Gebze, Kocaeli 41480 Turkey Made in Turkey www.flormar.com
A Cream that creates the appearance of all day skin perfection with sensorial comfort. Extreme wearing, light texture adapts to the skin's movements with a medium to high covering film. Glides on with a velvet soft feel that stays lightweight, soft and smooth. Application: Wash and rinse your latex sponge when you are finished with your application. Before you put your latex sponge into the container, be sure that it is dried. Keep away from direct sunlight and keep in a cool place. After use, close the cap properly. To report a serious adverse event contact [917] 768-7350

PACKAGE LABEL

flormar REBORN BB CREAM SUNSCREEN BROAD SPECTRUM SPF 30 Net Wt. 0.42 oz (12 g)

Product Labels

Enter section text here